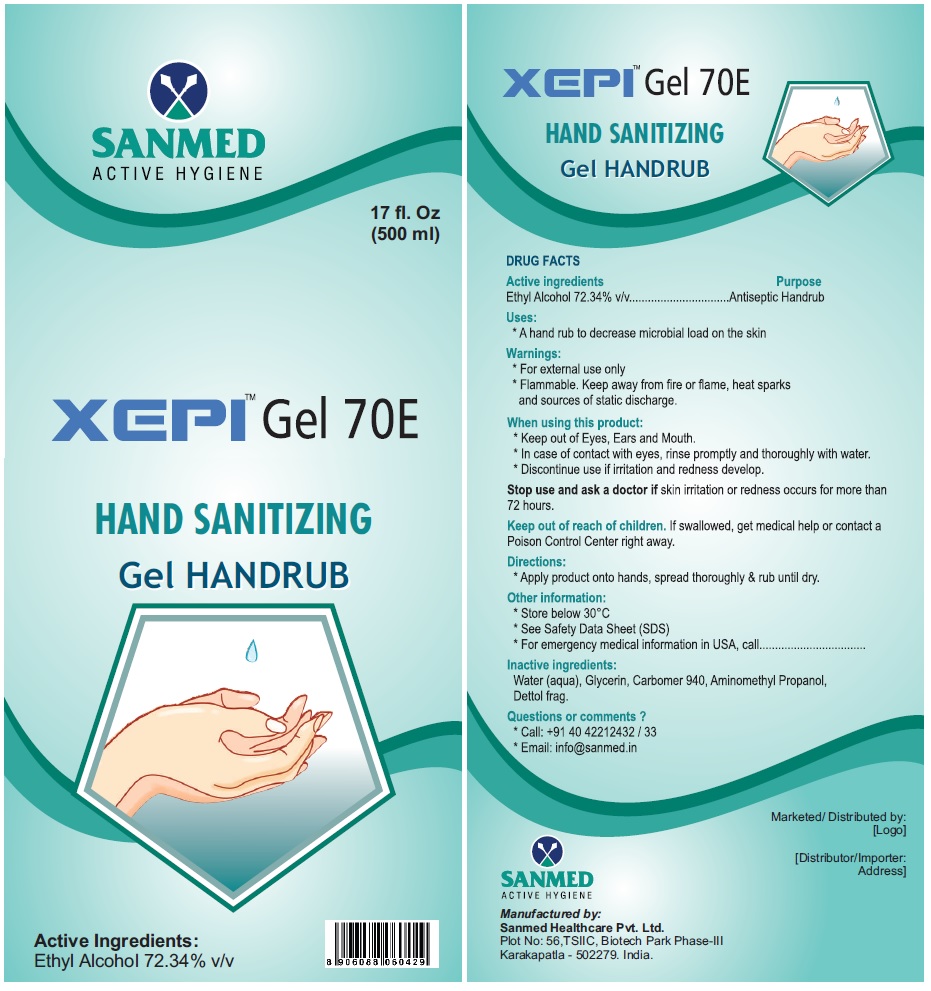 DRUG LABEL: XEPI Gel 70E HAND SANITIZING HANDRUB
NDC: 81357-102 | Form: GEL
Manufacturer: Sanmed Healthcare Private Limited
Category: otc | Type: HUMAN OTC DRUG LABEL
Date: 20201229

ACTIVE INGREDIENTS: ALCOHOL 72.34 mL/100 mL
INACTIVE INGREDIENTS: WATER; GLYCERIN; CARBOMER 940; AMINOMETHYLPROPANOL

SANMED ACTIVE HYGIENE
XEPITM Gel 70E HAND SANITIZING Gel HANDRUB

Active ingredients

Ethyl Alcohol 72.34% v/v

Purpose

Antiseptic Handrub

Uses:

* A hand rub to decrease microbial load on the skin

Warnings:

* For external use only

* Flammable. Keep away from fire or flame, heat sparks and sources of static discharge.

When using this product:

* Keep out of Eyes, Ears and Mouth.

* In case of contact with eyes, rinse promptly & thoroughly with water.

* Discontinue use if irritation and redness develop.

Stop use and ask a doctor if skin irritation or redness occurs for more than 72 hours.

Keep out of reach of children. If swallowed, get medical help or contact a Poison Control Center right away.

Directions:

* Apply product onto hands, spread thoroughly & rub until dry.

Other information:

* Store below 30°C

* See Safety Data Sheet (SDS)

* For emergency medical information in USA, call ..........................

Inactive ingredients:

Water (aqua), Glycerin, Carbomer 940, Aminomethyl Propanol, Dettol frag.

Questions or comments ?

* Call: +91 40 42212432 / 33

* Email: info@sanmed.in

Manufactured by:

Sanmed Healthcare Pvt. Ltd.

Plot No: 56, TSIIC, Biotech Park Phase-III

Karakapatla - 502279. India.